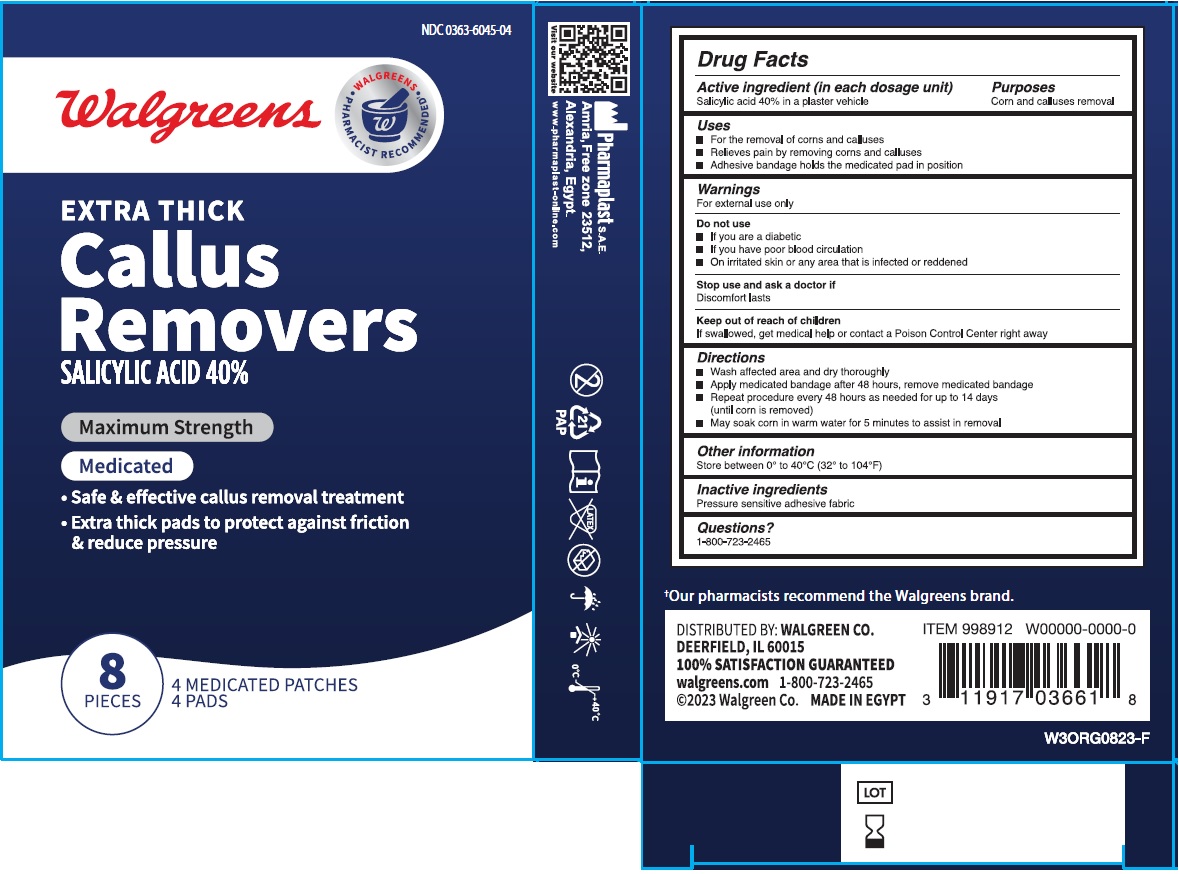 DRUG LABEL: Walgreens EXTRA THICK Callus Removers
NDC: 0363-6045 | Form: PATCH
Manufacturer: Walgreen Co.
Category: otc | Type: HUMAN OTC DRUG LABEL
Date: 20251231

ACTIVE INGREDIENTS: SALICYLIC ACID 0.23 g/1 1
INACTIVE INGREDIENTS: POLYACRYLATE-13

Walgreens EXTRA THICK Callus Removers

Active ingredient (in each dosage unit)

Salicylic acid 40% in a plaster vehicle

Purposes

Corn and calluses removal

Uses

• For the removal of corns and calluses
• Relieves pain by removing corns and calluses
• Adhesive bandage holds the medicated pad in position

Warnings

For external use only

Do not use
• If you are a diabetic
• If you have poor blood circulation
• On irritated skin or any area that is infected or reddened

Stop use and ask a doctor if
Discomfort lasts

Keep out of reach of children
If swallowed, get medical help or contact a Poison Control Center right away

Directions

• Wash affected area and dry thoroughly
• Apply medicated bandage after 48 hours, remove medicated bandage
• Repeat procedure every 48 hours as needed for up to 14 days (until corn is removed)
• May soak corn in warm water for 5 minutes to assist in removal

Other information

Store between 0° to 40°C (32° to 104°F)

Inactive ingredients

Pressure sensitive adhesive fabric

Questions?

1-800-723-2465

Maximum Strength

• Safe & effective callus removal treatment
• Extra thick pads to protect against friction & reduce pressure

4 MEDICATED PATCHES
4 PADS

Pharmaplast S.A.E.
Amria, Free zone 23512,
Alexandria, Egypt.
www.pharmaplast-online.com

†Our pharmacists recommend the Walgreens brand.

DISTRIBUTED BY: WALGREEN CO.
DEERFIELD, IL 60015
100% SATISFACTION GUARANTEED
walgreens.com
©2023 Walgreen Co. MADE IN EGYPT